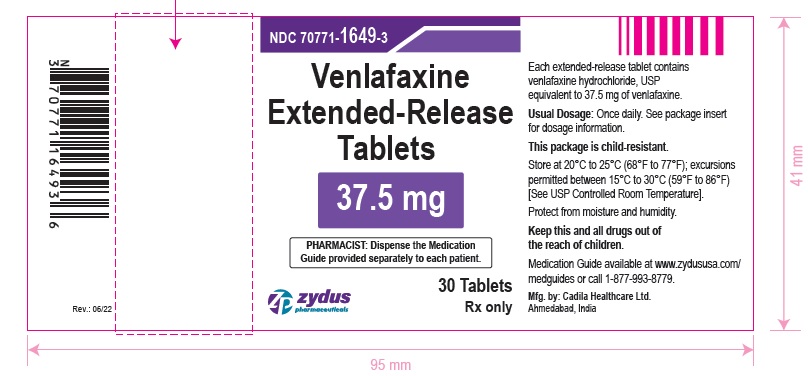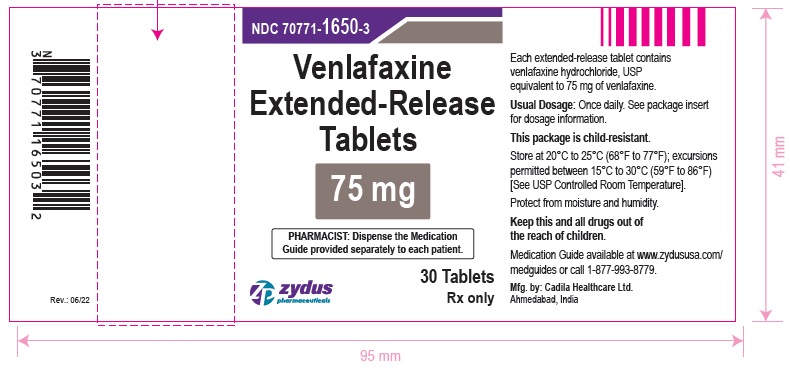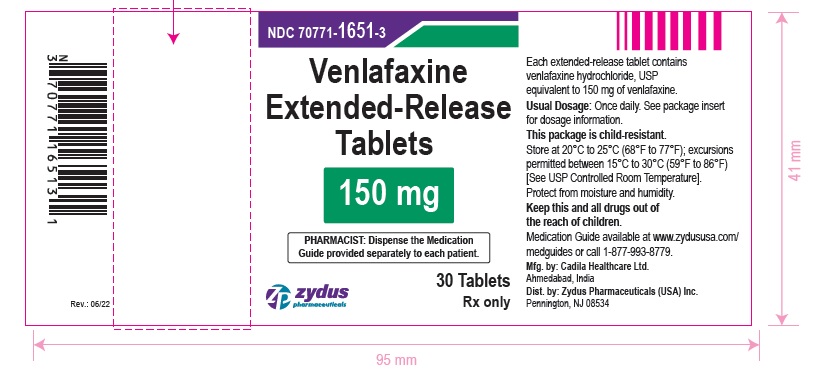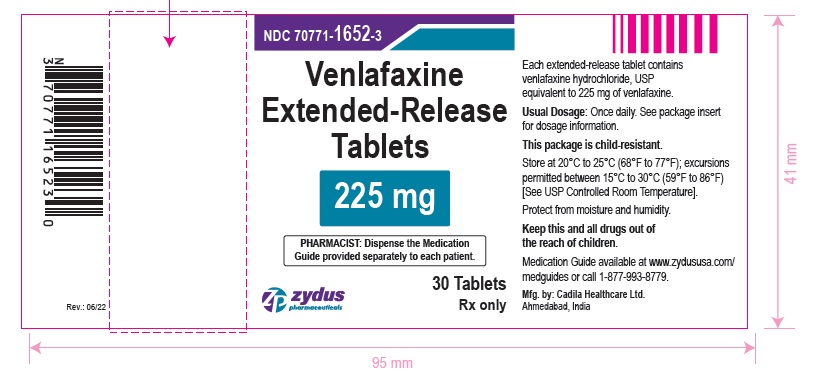 DRUG LABEL: Venlafaxine
NDC: 70771-1649 | Form: TABLET, EXTENDED RELEASE
Manufacturer: Zydus Lifesciences Limited
Category: prescription | Type: HUMAN PRESCRIPTION DRUG LABEL
Date: 20230928

ACTIVE INGREDIENTS: VENLAFAXINE HYDROCHLORIDE 37.5 mg/1 1
INACTIVE INGREDIENTS: CELLULOSE ACETATE; FERROSOFERRIC OXIDE; HYPROMELLOSE 2208 (100 MPA.S); MAGNESIUM STEARATE; MANNITOL; MICROCRYSTALLINE CELLULOSE; POLYETHYLENE GLYCOL 400; POVIDONE K90; PROPYLENE GLYCOL; SHELLAC; SILICON DIOXIDE

VENLAFAXINE extended-release tablets, for oral use

PACKAGE LABEL.PRINCIPAL DISPLAY PANEL

Venlafaxine extended-release tablets, 37.5 mg

NDC 70771-1649-3

30 Tablets

Rx only

Venlafaxine extended-release tablets, 75 mg

NDC 70771-1650-3

30 Tablets

Rx only

Venlafaxine extended-release tablets, 150 mg

NDC 70771-1651-3

30 Tablets

Rx only

Venlafaxine extended-release tablets, 225 mg

NDC 70771-1652-3

30 Tablets

Rx only